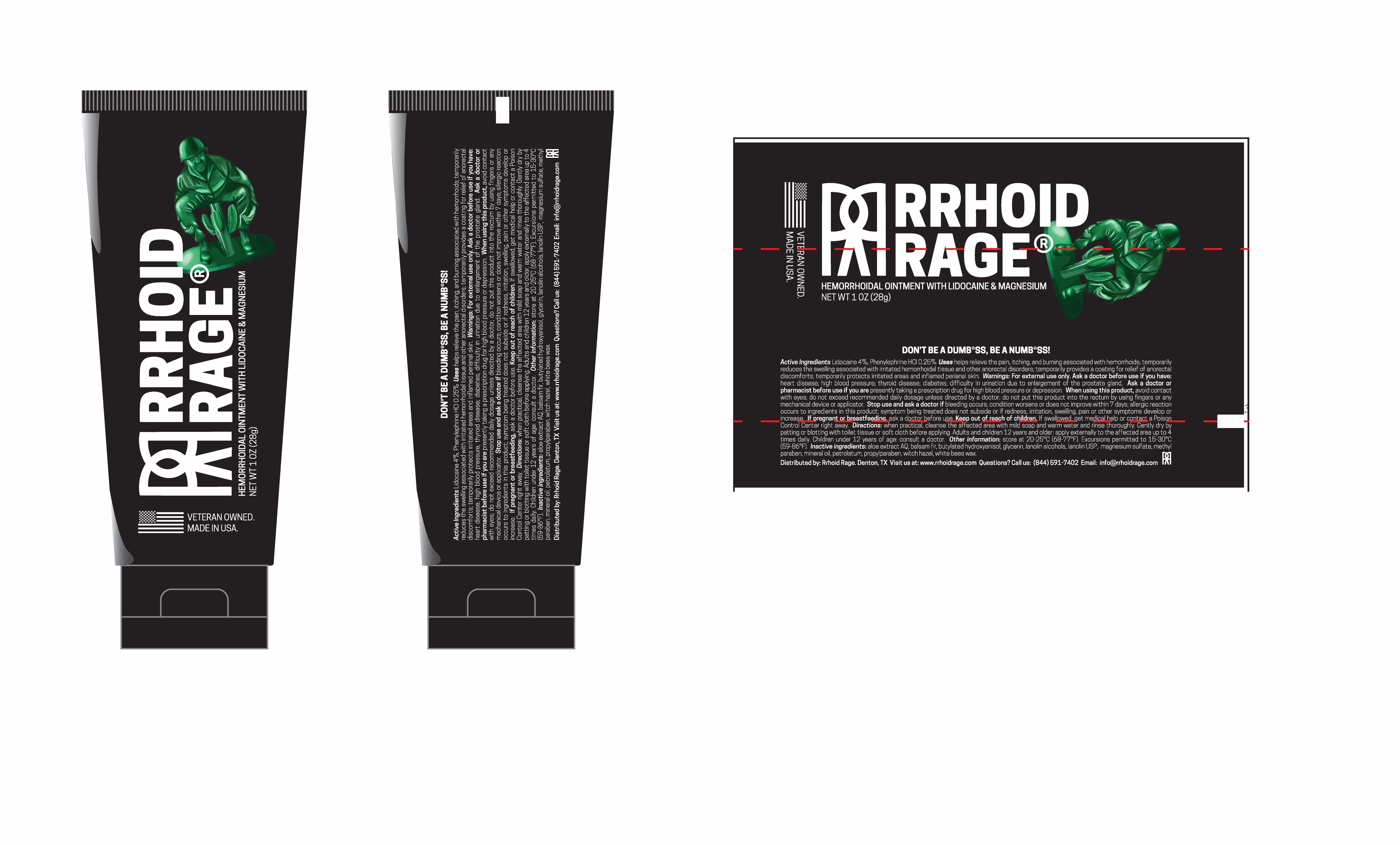 DRUG LABEL: Hemorrhoidal-Ointment
NDC: 82433-101 | Form: OINTMENT
Manufacturer: Rrhoid Rage
Category: otc | Type: HUMAN OTC DRUG LABEL
Date: 20220606

ACTIVE INGREDIENTS: LIDOCAINE 4 g/100 g; PHENYLEPHRINE HYDROCHLORIDE 0.25 g/100 g
INACTIVE INGREDIENTS: BALSAM FIR LEAFY TWIG; MAGNESIUM SULFATE, UNSPECIFIED; LANOLIN; LANOLIN ALCOHOLS; BUTYLATED HYDROXYANISOLE; ALOE; SYNTHETIC BEESWAX; GLYCERIN; WITCH HAZEL; METHYLPARABEN; MINERAL OIL; PETROLATUM; PROPYLPARABEN

Rrhoid Rage hemorrhoidal Ointment

ACTIVE INGREDIENT

Lidocaine 4%..................................................Local Anesthetic

Phenylephrine Hydrochloride 0.25%...............Vasoconstrictor

PURPOSE

Local anesthetic, Vasoconstrictor

INDICATIONS AND USAGE

-Helps relieve the pain, itching, and burning associated with hemorrhoids.

-Temporarily reduces the swelling associated with irritated hemorrhoidal
tissue and other anorectal disorders.
-Temporarily provides a coating for relief of anorectal discomforts.
-Temporarily protects irritated areas and inflamed perianal skin.

WARNINGS

For external and/or intrarectal use only.

Ask a doctor before use if you have:
-Heart disease; high blood pressure; thyroid disease; diabetes.
-Difficulty in urination due to enlargement of the prostate gland.

Ask a doctor or pharmacist before use if you are presently taking a prescription drug for high
blood pressure or depression.

When using this product
-Avoid contact with eyes.
-Do not exceed recommended daily dosage unless directed by a doctor.
-Do not put this product into the rectum by using fingers or any mechanical device or applicator.

Stop use and ask a doctor if
-Bleeding occurs.
-Condition worsens or does not improve within 7 days.
-Allergic reaction occurs to ingredients in this product.
-Symptom being treated does not subside or if redness, irritation, swelling,
pain or other symptoms develop or increase.

If pregnant or breastfeeding, ask a doctor before use.

Keep out of reach of children. If swallowed, get medical help or contact a
Poison Control Center right away.

DOSAGE AND ADMINISTRATION

-When practical, cleanse the affected area with mild soap and warm water and rinse thoroughly.
Gently dry by patting or blotting with toilet tissue or soft cloth before applying.
-Adults and children 12 years and older: apply externally to the affected area up to 4 times daily.
-Children under 12 years of age: consult a doctor.

Other information
-Store at 20-25°C (68-77°F). Excursions permitted to 15-30°C (59-86°F).

INACTIVE INGREDIENT

aloe extract AQ, balsam fir, butylated hydroxyanisol, glycerin, lanolin alcohols, lanolin USP,
magnesium sulfate, methyl paraben, mineral oil, petrolatum, propylparaben, witch hazel, white
bees wax.